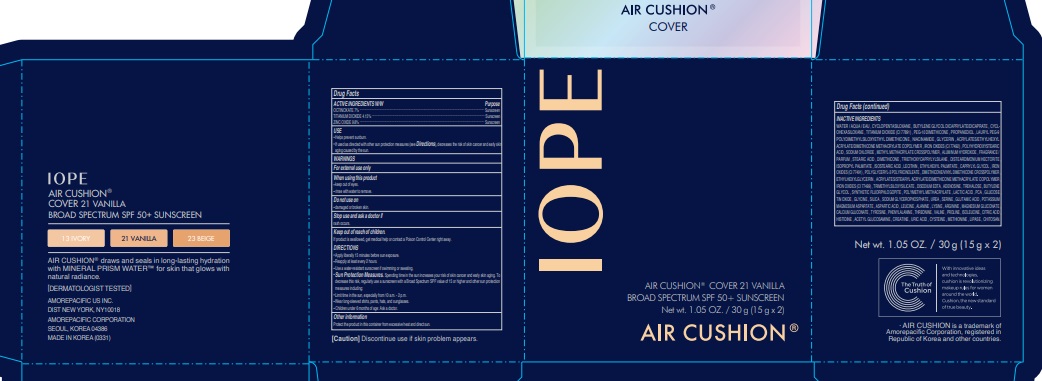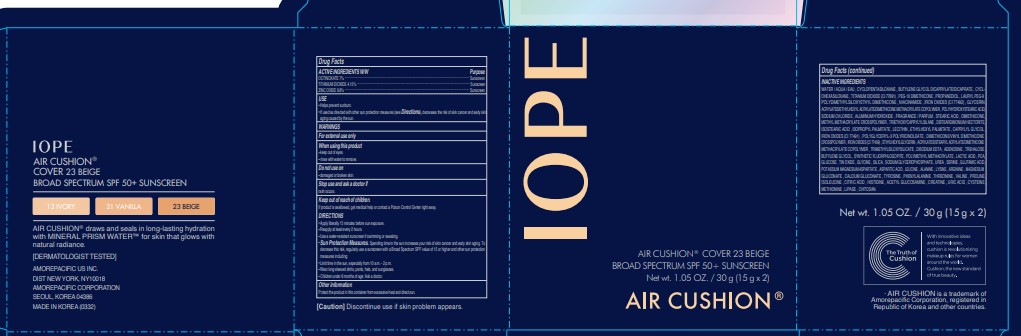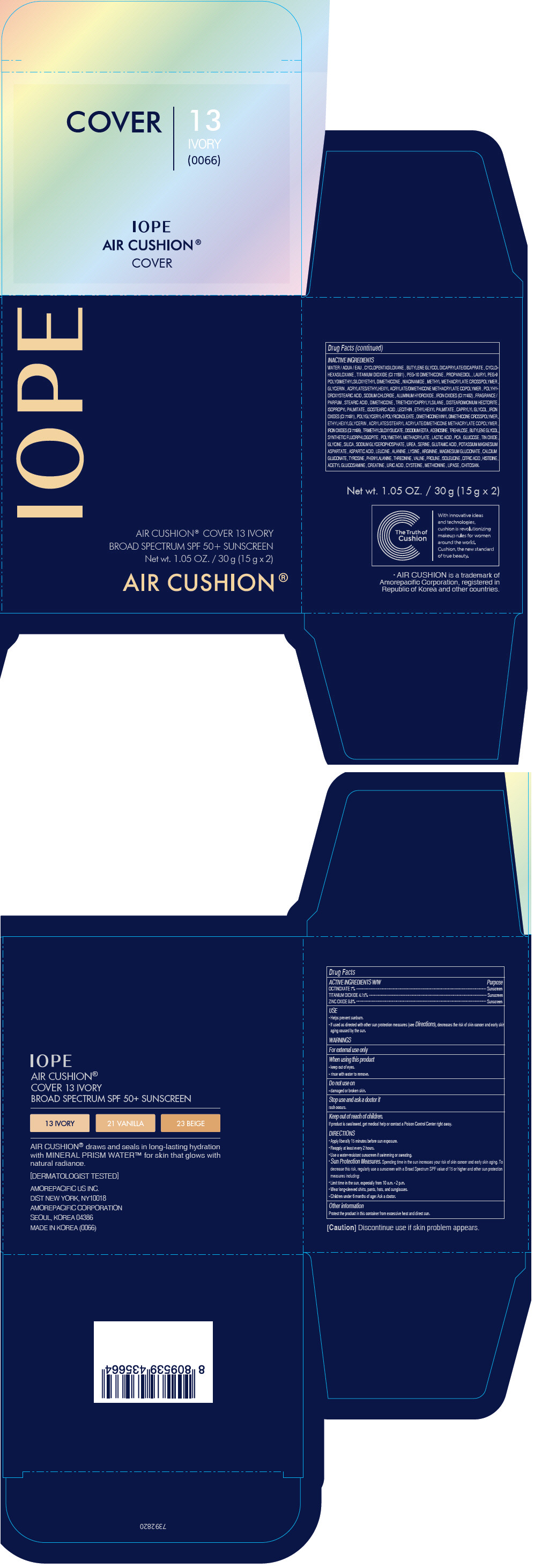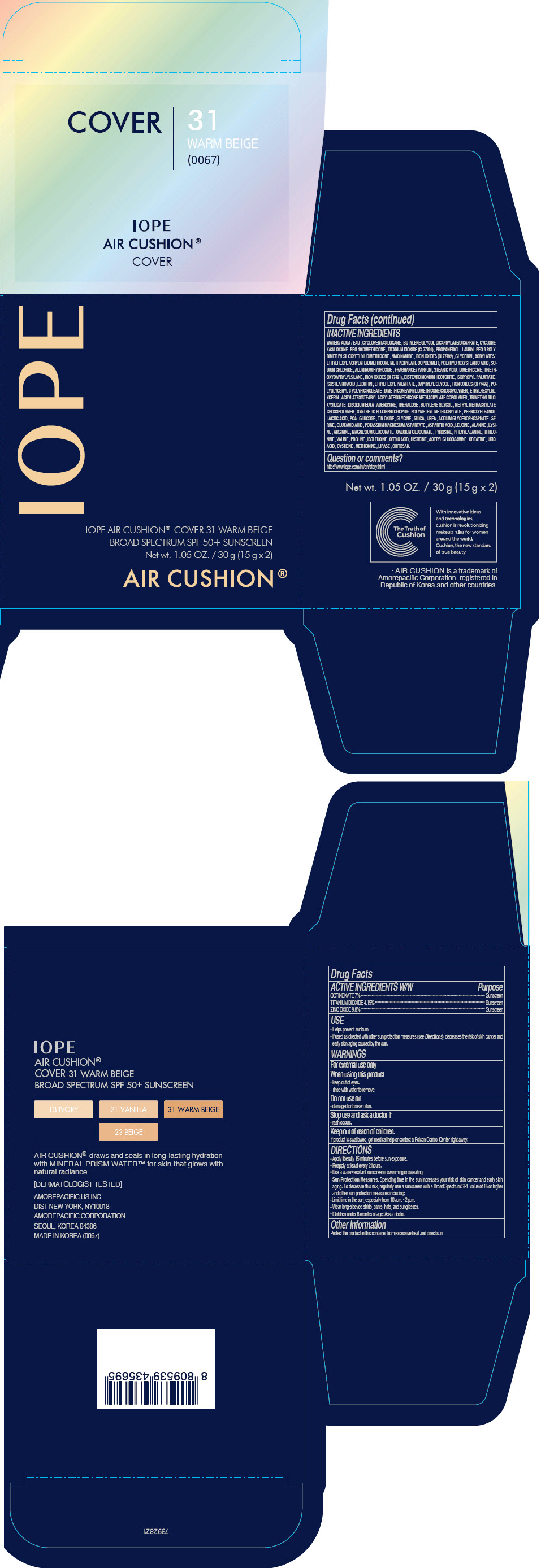 DRUG LABEL: IOPE AIR CUSHION Cover 13 Ivory
NDC: 43419-403 | Form: LOTION
Manufacturer: AMOREPACIFIC CORPORATION
Category: otc | Type: HUMAN OTC DRUG LABEL
Date: 20241008

ACTIVE INGREDIENTS: ZINC OXIDE 2.94 g/30 g; OCTINOXATE 2.1 g/30 g; TITANIUM DIOXIDE 1.245 g/30 g
INACTIVE INGREDIENTS: FERRIC OXIDE RED; ETHYLHEXYLGLYCERIN; FERROSOFERRIC OXIDE; EDETATE DISODIUM ANHYDROUS; ADENOSINE; TREHALOSE; BUTYLENE GLYCOL; POLY(METHYL METHACRYLATE; 450000 MW); PIDOLIC ACID; LACTIC ACID, UNSPECIFIED FORM; DEXTROSE, UNSPECIFIED FORM; STANNIC OXIDE; GLYCINE; SILICON DIOXIDE; UREA; SODIUM GLYCEROPHOSPHATE; SERINE; GLUTAMIC ACID; POTASSIUM MAGNESIUM ASPARTATE; ASPARTIC ACID; LEUCINE; ALANINE; LYSINE; ARGININE; CALCIUM GLUCONATE; MAGNESIUM GLUCONATE; TYROSINE; PHENYLALANINE; PROLINE; THREONINE; VALINE; ISOLEUCINE; CITRIC ACID MONOHYDRATE; HISTIDINE; N-ACETYLGLUCOSAMINE; CREATINE; URIC ACID; CYSTEINE; METHIONINE; WATER; CYCLOMETHICONE 5; BUTYLENE GLYCOL DICAPRYLATE/DICAPRATE; CYCLOMETHICONE 6; PEG-10 DIMETHICONE (600 CST); PROPANEDIOL; LAURYL PEG-9 POLYDIMETHYLSILOXYETHYL DIMETHICONE; NIACINAMIDE; GLYCERIN; SODIUM CHLORIDE; ALUMINUM HYDROXIDE; FERRIC OXIDE YELLOW; STEARIC ACID; DIMETHICONE; TRIETHOXYCAPRYLYLSILANE; DISTEARDIMONIUM HECTORITE; ETHYLHEXYL PALMITATE; ISOSTEARIC ACID; ISOPROPYL PALMITATE; CAPRYLYL GLYCOL

IOPE AIR CUSHION® Cover

Drug Facts

ACTIVE INGREDIENT

ACTIVE INGREDIENTS W/W | Purpose
OCTINOXATE 7% | Sunscreen
TITANIUM DIOXIDE 4.15% | Sunscreen
ZINC OXIDE 9.8% | Sunscreen

USE

- Helps prevent sunburn.
- If used as directed with other sun protection measures (see Directions), decreases the risk of skin cancer and early skin aging caused by the sun.

WARNINGS

For external use only

When using this product

- keep out of eyes.
- rinse with water to remove.

Do not use on

- damaged or broken skin.

Stop use and ask a doctor if

rash occurs.

Keep out of reach of children.

If product is swallowed, get medical help or contact a Poison Control Center right away.

DIRECTIONS

- Apply liberally 15 minutes before sun exposure.
- Reapply at least every 2 hours.
- Use a water-resistant sunscreen if swimming or sweating.
- Sun Protection Measures. Spending time in the sun increases your risk of skin cancer and early skin aging. To decrease this risk, regularly use a sunscreen with a Broad Spectrum SPF value of 15 or higher and other sun protection measures including:
  - Limit time in the sun, especially from 10 a.m. - 2 p.m.
  - Wear long-sleeved shirts, pants, hats, and sunglasses.
- Children under 6 months of age: Ask a doctor.

Other information

Protect the product in this container from excessive heat and direct sun.

INACTIVE INGREDIENTS

WATER / AQUA / EAU , CYCLOPENTASILOXANE , BUTYLENE GLYCOL DICAPRYLATE/DICAPRATE , CYCLOHEXASILOXANE , TITANIUM DIOXIDE (CI 77891) , PEG-10 DIMETHICONE , PROPANEDIOL , LAURYL PEG-9 POLYDIMETHYLSILOXYETHYL DIMETHICONE , NIACINAMIDE , METHYL METHACRYLATE CROSSPOLYMER , GLYCERIN , ACRYLATES/ETHYLHEXYL ACRYLATE/DIMETHICONE METHACRYLATE COPOLYMER , POLYHYDROXYSTEARIC ACID , SODIUM CHLORIDE , ALUMINUM HYDROXIDE , IRON OXIDES (CI 77492) , FRAGRANCE / PARFUM , STEARIC ACID , DIMETHICONE , TRIETHOXYCAPRYLYLSILANE , DISTEARDIMONIUM HECTORITE , ISOPROPYL PALMITATE , ISOSTEARIC ACID , LECITHIN , ETHYLHEXYL PALMITATE , CAPRYLYL GLYCOL , IRON OXIDES (CI 77491) , POLYGLYCERYL-3 POLYRICINOLEATE , DIMETHICONE/VINYL DIMETHICONE CROSSPOLYMER , ETHYLHEXYLGLYCERIN , ACRYLATES/STEARYL ACRYLATE/DIMETHICONE METHACRYLATE COPOLYMER , RON OXIDES (CI 77499) , TRIMETHYLSILOXYSILICATE , DISODIUM EDTA , ADENOSINE , TREHALOSE , BUTYLENE GLYCOL , SYNTHETIC FLUORPHLOGOPITE , POLYMETHYL METHACRYLATE , LACTIC ACID , PCA , GLUCOSE , TIN OXIDE , GLYCINE , SILICA , SODIUM GLYCEROPHOSPHATE , UREA , SERINE , GLUTAMIC ACID , POTASSIUM MAGNESIUM ASPARTATE , ASPARTIC ACID , LEUCINE , ALANINE , LYSINE , ARGININE , MAGNESIUM GLUCONATE , CALCIUM GLUCONATE , TYROSINE , PHENYLALANINE , THREONINE , VALINE , PROLINE , ISOLEUCINE , CITRIC ACID , HISTIDINE , ACETYL GLUCOSAMINE , CREATINE , URIC ACID , CYSTEINE , METHIONINE , LIPASE , CHITOSAN.

PRINCIPAL DISPLAY PANEL - 15 g Container Carton - 13 Ivory

IOPE

AIR CUSHION® COVER 13 IVORY
BROAD SPECTRUM SPF 50+ SUNSCREEN
Net wt. 1.05 OZ. / 30 g (15 g x 2)

AIR CUSHION®

PRINCIPAL DISPLAY PANEL - 15 g Container Carton - 21 Vanilla

IOPE

AIR CUSHION® COVER 21 VANILLA
BROAD SPECTRUM SPF 50+ SUNSCREEN
Net wt. 1.05 OZ. / 30 g (15 g x 2)

AIR CUSHION®

PRINCIPAL DISPLAY PANEL - 15 g Container Carton - 23 Beige

IOPE

AIR CUSHION® COVER 23 BEIGE
BROAD SPECTRUM SPF 50+ SUNSCREEN
Net wt. 1.05 OZ. / 30 g (15 g x 2)

AIR CUSHION®

PRINCIPAL DISPLAY PANEL - 15 g Container Carton - 31 Warm Beige

IOPE

IOPE AIR CUSHION® COVER 31 WARM BEIGE
BROAD SPECTRUM SPF 50+ SUNSCREEN
Net wt. 1.05 OZ. / 30 g (15 g x 2)

AIR CUSHION®